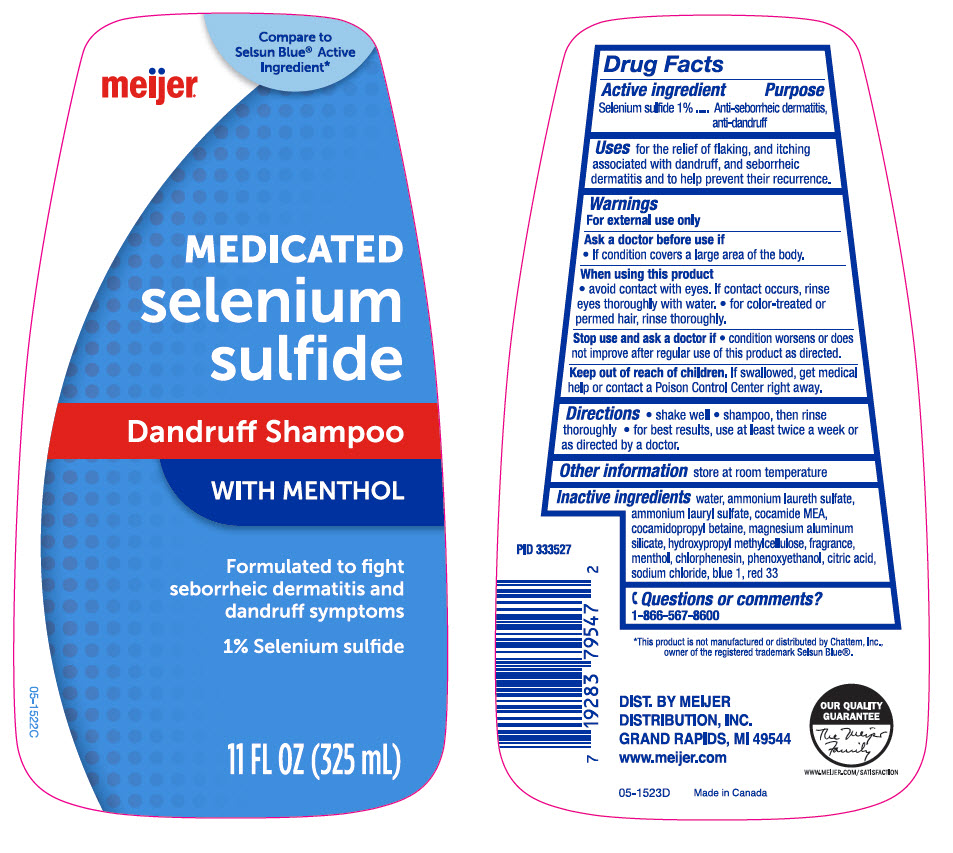 DRUG LABEL: Meijer Medicated Selenium Sulfide
NDC: 41250-545 | Form: SHAMPOO
Manufacturer: Meijer Distribution, Inc
Category: otc | Type: HUMAN OTC DRUG LABEL
Date: 20250114

ACTIVE INGREDIENTS: Selenium Sulfide 10 mg/1 mL
INACTIVE INGREDIENTS: Water; Ammonium Laureth-5 Sulfate; Ammonium Lauryl Sulfate; Cocamidopropyl Betaine; Coco Monoethanolamide; Magnesium Aluminum Silicate; Hypromellose, Unspecified; Menthol, Unspecified Form; Chlorphenesin; Phenoxyethanol; Citric Acid Monohydrate; Sodium Chloride; Fd&C Blue No. 1; D&C Red No. 33

Meijer® Medicated Selenium Sulfide Dandruff Shampoo
Anti-Dandruff

Drug Facts

Active ingredient

Selenium Sulfide 1%

Purpose

Anti-seborrheic dermatitis, anti-dandruff

Uses

for the relief of flaking, and itching associated with dandruff, and seborrheic dermatitis, and to help prevent their recurrence.

Warnings

For external use only

As a doctor before use if

- If condition covers a large area of the body.

When using this product

- avoid contact with the eyes. If contact occurs, rinse eyes thoroughly with water.
- for color-treated or permed hair, rinse thoroughly.

Stop use and ask a doctor if

- condition worsens or does not improve after regular use of this product as directed.

Keep out of reach of children. If swallowed, get medical help or contact a Poison Control Center right away.

Directions

- shake well
- shampoo, then rinse thoroughly
- for best results, use at least twice a week or as directed by a doctor.

Other information

store at room temperature

Inactive ingredients

water, ammonium laureth sulfate, ammonium lauryl sulfate, cocamide MEA, cocamidopropyl betaine, magnesium aluminum silicate, hydroxypropyl methylcellulose, fragrance, menthol, chlorphenesin, phenoxyethanol, citric acid, sodium chloride, blue 1, red 33

Questions or comments?

1-866-567-8600

DIST. BY MEIJER
DISTRIBUTION, INC.
GRAND RAPIDS, MI 49544

PRINCIPAL DISPLAY PANEL - 325 mL Bottle Label

Compare to
Selsun Blue® Active
Ingredient*

meijer®

MEDICATED
selenium
sulfide

Dandruff Shampoo
WITH MENTHOL

Formulated to fight
seborrheic dermatitis and
dandruff symptoms

1% Selenium sulfide

11 FL OZ (325 mL)

05-1522C